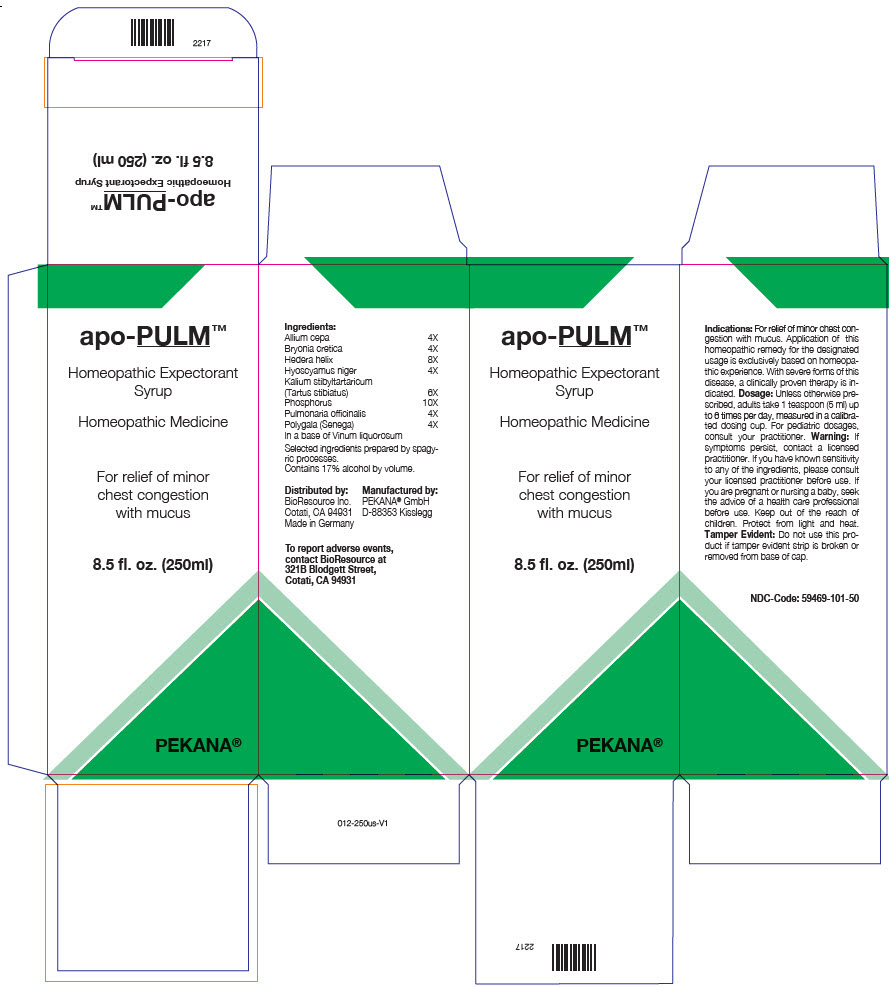 DRUG LABEL: apo-PULM
NDC: 59469-101 | Form: SYRUP
Manufacturer: PEKANA Naturheilmittel GmbH
Category: homeopathic | Type: HUMAN OTC DRUG LABEL
Date: 20221205

ACTIVE INGREDIENTS: Onion 4 [hp_X]/125 mL; Bryonia Dioica Root 4 [hp_X]/125 mL; Hedera helix Flowering Twig 8 [hp_X]/125 mL; Hyoscyamus Niger 4 [hp_X]/125 mL; Phosphorus 10 [hp_X]/125 mL; Polygala senega Root 4 [hp_X]/125 mL; Antimony potassium tartrate 6 [hp_X]/125 mL; Pulmonaria officinalis Whole 4 [hp_X]/125 mL
INACTIVE INGREDIENTS: Water; Alcohol

apo-PULM™

ACTIVE INGREDIENT

Ingredients:
Allium cepa | 4X
Bryonia cretica | 4X
Hedera helix | 8X
Hyoscyamus niger | 4X
Kalium stibyltartaricum (Tartus stibiatus) | 6X
Phosphorus | 10X
Pulmonaria officinalis | 4X
Polygala (Senega) | 4X

In a base of Vinum liquorosum.

Selected ingredients prepared by spagyric processes.

INACTIVE INGREDIENT

Contains 17% alcohol by volume.

Indications

PURPOSE

For relief of minor chest congestion with mucus. Application of this homeopathic remedy for the designated usage is exclusively based on homeopathic experience. With severe forms of this disease, a clinically proven therapy is indicated.

Dosage

Unless otherwise prescribed, adults take 1 teaspoon up to 6 times per day. For pediatric dosages, consult your practitioner.

Warning

ASK DOCTOR

If symptoms persist, contact a licensed practitioner. If you have known sensitivity to any of the ingredients, please consult your licensed practitioner before use. If you are pregnant or nursing a baby, seek the advice of a health care professional before use.

Keep out of the reach of children.

STORAGE AND HANDLING

Protect from light and heat.

Tamper Evident

Do not use this product if tamper evident strip is broken or removed from base of cap.

QUESTIONS

To report adverse events, contact BioResource at 321B Blodgett Street, Cotati, CA 94931

Distributed by:
BioResource Inc.
Cotati, CA 94931

Manufactured by:
PEKANA® GmbH
D-88353 Kisslegg

PRINCIPAL DISPLAY PANEL - 250 ml Bottle Box

apo-PULM™

Homeopathic Expectorant
Syrup

Homeopathic Medicine

For relief of minor
chest congestion
with mucus

8.5 fl. oz. (250ml)

PEKANA®